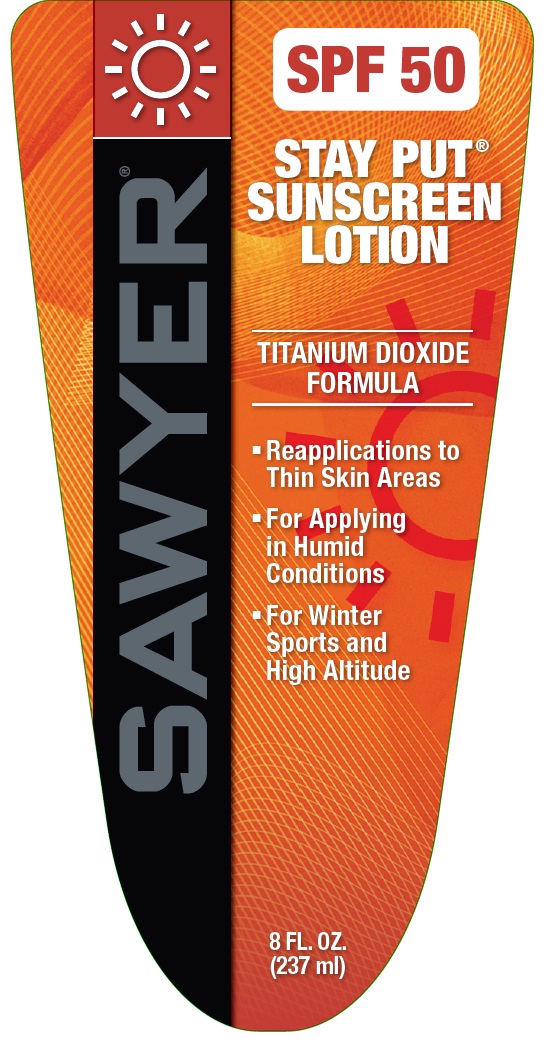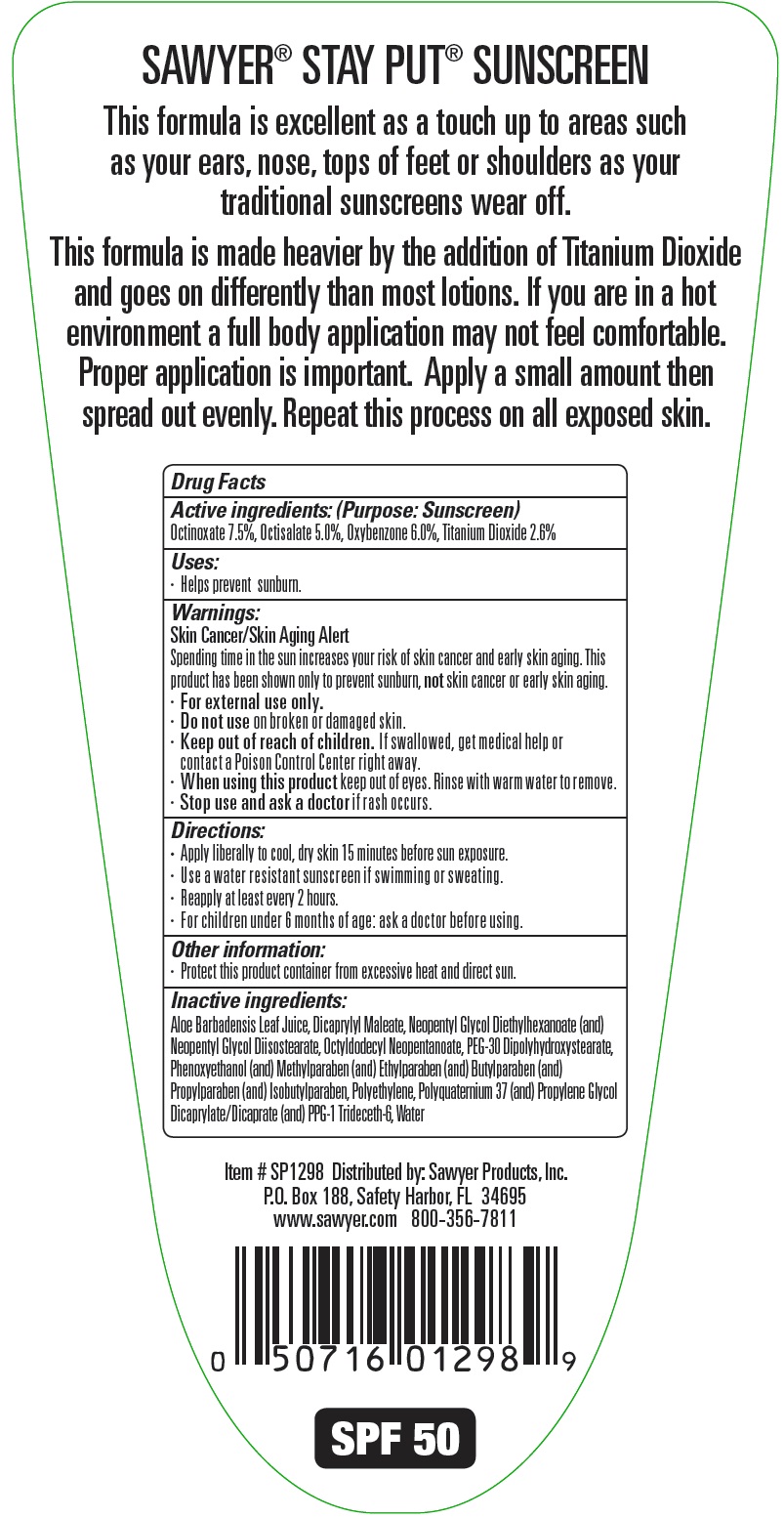 DRUG LABEL: SPF 50 Stay Put Sunscreen
NDC: 70392-015 | Form: LOTION
Manufacturer: Sawyer Products
Category: otc | Type: HUMAN OTC DRUG LABEL
Date: 20160115

ACTIVE INGREDIENTS: OCTINOXATE 75 mg/1 mL; OCTISALATE 50 mg/1 mL; OXYBENZONE 60 mg/1 mL; TITANIUM DIOXIDE 26 mg/1 mL
INACTIVE INGREDIENTS: ALOE VERA LEAF; DIOCTYL MALEATE; NEOPENTYL GLYCOL DIETHYLHEXANOATE; NEOPENTYL GLYCOL DIISOSTEARATE; OCTYLDODECYL NEOPENTANOATE; PEG-30 DIPOLYHYDROXYSTEARATE; PHENOXYETHANOL; METHYLPARABEN; ETHYLPARABEN; BUTYLPARABEN; PROPYLPARABEN; ISOBUTYLPARABEN; HIGH DENSITY POLYETHYLENE; PROPYLENE GLYCOL; PPG-1 TRIDECETH-6; WATER

SPF 50 Stay Put Sunscreen

Active ingredients:

Octinoxate 7.5%, Octisalate 5.0%, Oxybenzone 6.0%, Titanium Dioxide 2.6%

Purpose:

Sunscreen

Uses:

· Helps prevent sunburn.

Warnings:

Skin Cancer/Skin Aging Alert
Spending time in the sun increases your risk of skin cancer and early skin aging. This product has been shown only to prevent sunburn, not skin cancer or early skin aging.
· For external use only.

Do not use

on broken or damaged skin.

Keep out of reach of children.

If swallowed, get medical help or contact a Poison Control Center right away.

When using this product

keep out of eyes. Rinse with warm water to remove.

Stop use and ask a doctor

if rash occurs.

Directions:

· Apply liberally to cool, dry skin 15 minutes before sun exposure.
· Use a water resistant sunscreen if swimming or sweating.
· Reapply at least every 2 hours.
· For children under 6 months of age: ask a doctor before using.

Other information:

· Protect this product container from excessive heat and direct sun.

Inactive ingredients:

Aloe Barbadensis Leaf Juice, Dicaprylyl Maleate, Neopentyl Glycol Diethylhexanoate (and) Neopentyl Glycol Diisostearate, Octyldodecyl Neopentanoate, PEG-30 Dipolyhydroxystearate, Phenoxyethanol (and) Methyl paraben (and) Ethylparaben (and) Butylparaben (and)
Propyl paraben (and) Isobutylparaben, Poly ethylene, Poly quaternium 37 (and) Propylene Glycol Dicaprylate/Dicaprate (and) PPG-1 Trideceth-6, Water